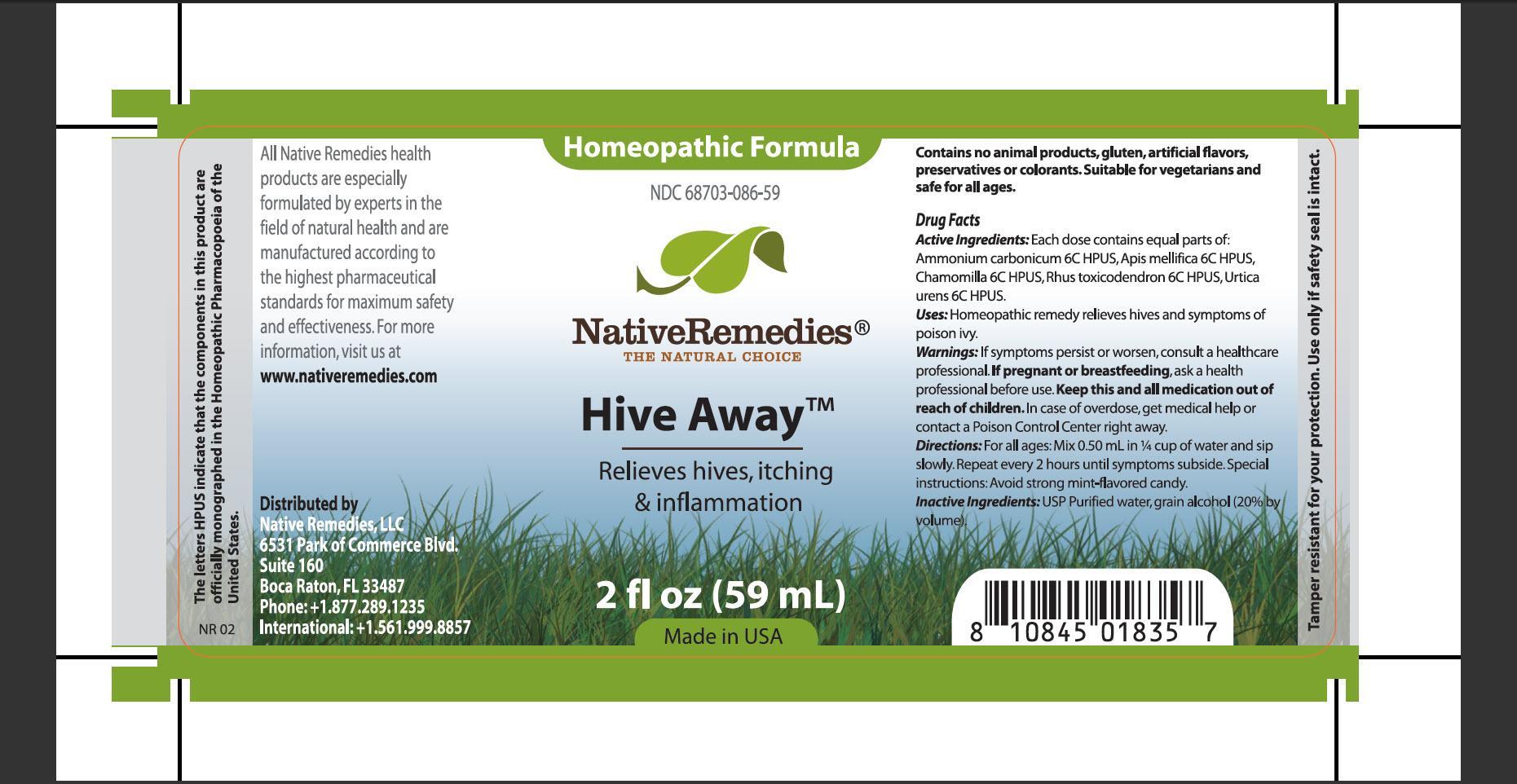 DRUG LABEL: Hive Away
NDC: 68703-086 | Form: TINCTURE
Manufacturer: Native Remedies, LLC
Category: homeopathic | Type: HUMAN OTC DRUG LABEL
Date: 20130411

ACTIVE INGREDIENTS: AMMONIUM CARBONATE 6 [hp_C]/1 mL; APIS MELLIFERA 6 [hp_C]/1 mL; MATRICARIA RECUTITA 6 [hp_C]/1 mL; TOXICODENDRON PUBESCENS LEAF  6 [hp_C]/1 mL; URTICA URENS 6 [hp_C]/1 mL
INACTIVE INGREDIENTS: WATER; ALCOHOL

Hive Away

PURPOSE

Relieves hives, itching and inflammation

ACTIVE INGREDIENT

Active Ingredients: Each dose contains equal parts of: Ammonium carbonicum 6C HPUS, Apis mellifica 6C HPUS, Chamomilla 6C HPUS, Rhus toxicodendron 6C HPUS, Urtica urens 6C HPUS

INDICATIONS AND USAGE

Uses: Homeopathic remedy relieves hives and symptoms of poison ivy

WARNINGS

Warnings: If symptoms persist or worsen, consult a healthcare professional

PREGNANCY OR BREAST FEEDING

If pregnant or breastfeeding, ask a health professional before use

KEEP OUT OF REACH OF CHILDREN

Keep this and all medication out of reach of children

OVERDOSAGE

In case of overdose, get medical help or contact Control Poison Center right away

DOSAGE AND ADMINISTRATION

Directions: For all ages: mix 0.50 mL in 1/4 cup of water and sip slowly. Repeat every 2 hours until symptoms subside. Special instructions: Avoid strong mint-flavored candy

INACTIVE INGREDIENT

Inactive Ingredients: USP Purified water, grain alcohol (20% by volume)

PATIENT COUNSELING INFORMATION

The letters HPUS indicate that the components in this product are officially monographed in the Homeopathic Pharmacopoeia of the United States

All Native Remedies health products are especially formulated by experts in the field of natural health and are manufactured according to the highest pharmaceutical standards for maximum safety and effectiveness. For more information, visit us at www.naticeremedies.com

Distributed by
Native Remedies, LLC
6531 Park of Commerce Blvd.
Suite 160
Boca Raton, FL 33487
Phone: +1.877.289.1235
International:+1.561.999.8857

Contains no animal products, gluten, artificial flavors, preservatives or colorants. Suitable for vegetarians and safe for all ages

STORAGE AND HANDLING

Tamper resistant for your protection. Use only if safety seal is intact